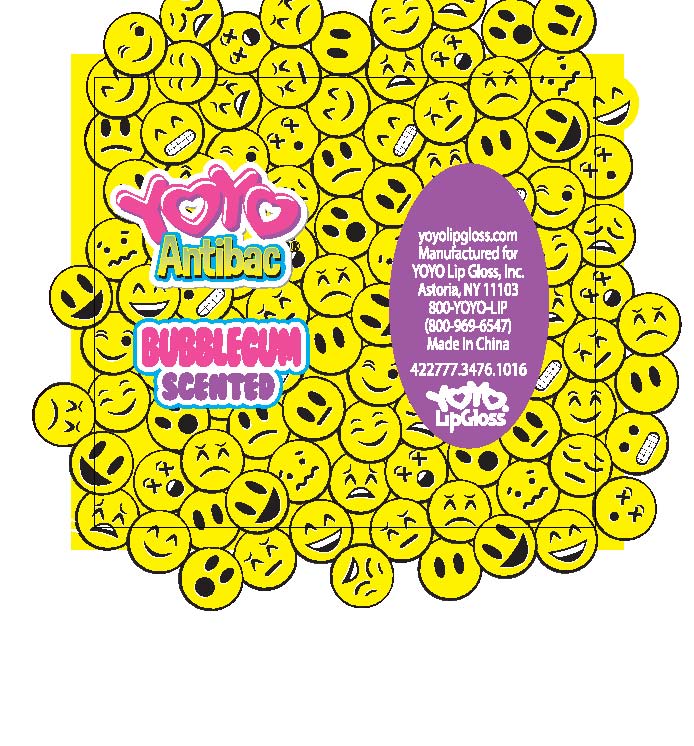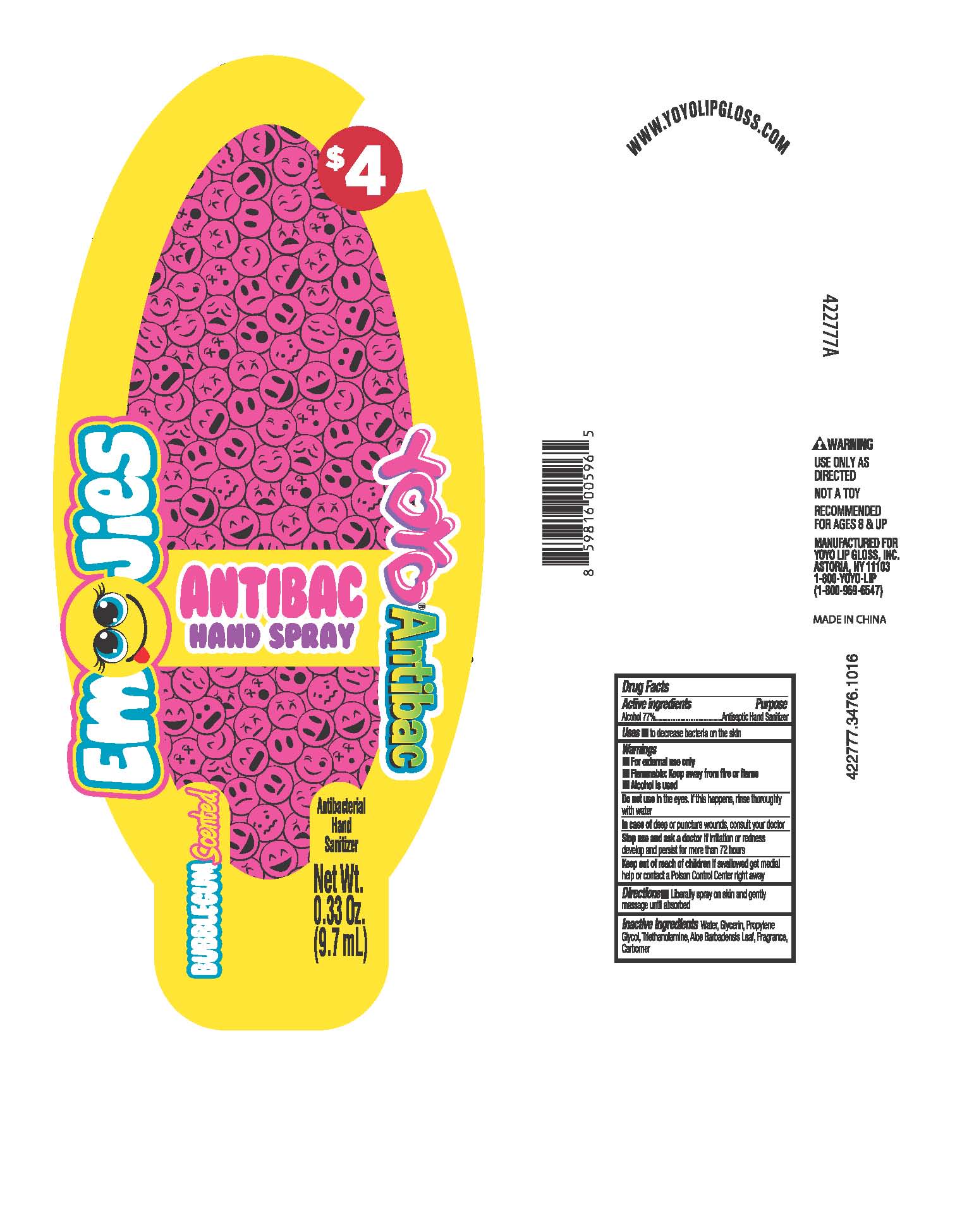 DRUG LABEL: Antibacterial Hand Sanitizer
NDC: 70611-004 | Form: GEL
Manufacturer: Yoyo Lip Gloss Inc.
Category: otc | Type: HUMAN OTC DRUG LABEL
Date: 20160819

ACTIVE INGREDIENTS: ALCOHOL 77 mL/100 mL
INACTIVE INGREDIENTS: WATER; ALOE VERA LEAF; GLYCERIN; PROPYLENE GLYCOL; CARBOMER INTERPOLYMER TYPE A (55000 CPS); TROLAMINE

Active ingredients
Alcohol 77%

Purpose
Antiseptic Hand Sanitizer

Warnings

For external use only

Flammable: Keep away from fire or flame

Alcohol is used

Do not use in the eyes. If this happens, rinse thoroughly with water.

In case of deep or puncture wounds, consult your doctor

Stop use and ask a doctor if irritation or redness develops and persists for more than 72 hours

Keep out of reach of children If swallowed get medical help or contact a Poison Control Center right away

Directions

Liberally spray on skin and gently massage until absorbed

INACTIVE INGREDIENT

Inactive Ingredients Water, Glycerin, Propylene Glycol, Triethanolamine, Aloe Barbadenis Leaf, Fragrance, Carbomer

Uses

to decrease bacteria on the skin